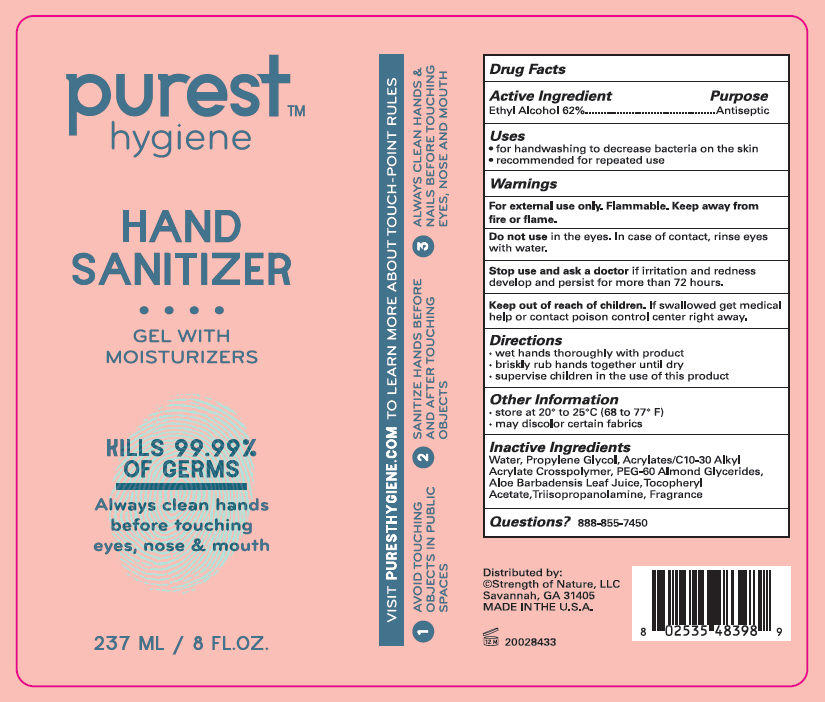 DRUG LABEL: Hand Sanitizer 
NDC: 74991-433 | Form: GEL
Manufacturer: Strength of Nature,LLC
Category: otc | Type: HUMAN OTC DRUG LABEL
Date: 20200420

ACTIVE INGREDIENTS: ALCOHOL 62 mL/100 mL
INACTIVE INGREDIENTS: PROPYLENE GLYCOL; WATER; PEG-60 ALMOND GLYCERIDES; ALOE VERA LEAF; .ALPHA.-TOCOPHEROL ACETATE; TRIISOPROPANOLAMINE; CARBOMER INTERPOLYMER TYPE B (ALLYL PENTAERYTHRITOL CROSSLINKED)

Hand Sanitizer
purest™ hygiene

Drug Facts

Active Ingredient

Ethyl Alcohol 62%

Purpose

Antiseptic

Uses

- for hand washing to decrease bacteria on the skin
- recommended for repeated use

Warnings

For external use only. Flammable. Keep away from fire or flame.

Do not use in the eyes. In case of contact, rinse eyes with water.

Stop use and ask a doctor if irritation and redness develop and persist for more than 72 hours.

Keep Out of reach of children. If swallowed get medical help or contact poison control center right away.

Directions

- wet hands thoroughly with product
- briskly rub hands together until dry
- Supervise children in the use of this product.

Other Information

- store at 20-25° C (68 to 77°F)
- may discolor certain fabrics

Inactive Ingredients

Water, Propylene Glycol, Acrylates/C10-3- Alkyl Acrylate Crosspolymer, PEG-60 Almond Glycerides, Aloe Barbadensis Leaf Juice, Tocopheryl Acetate, Triisopropanolamine, Fragrance

Questions?

888-855-7450

Distributed by:
©Strength of Nature, LLC
Savannah, GA 31405

PRINCIPAL DISPLAY PANEL - 237 ML Bottle Label

purest™
hygiene

HAND
SANITIZER

GEL WITH
MOISTURIZERS

KILLS 99.99%
OF GERMS

Always clean hands
before touching
eyes, nose & mouth

237 ML / 8 FL.OZ.